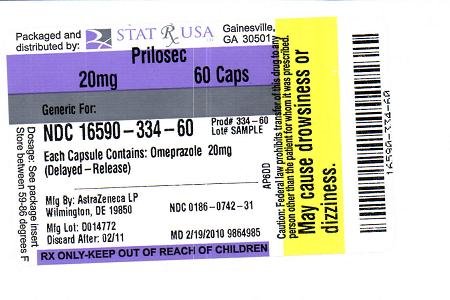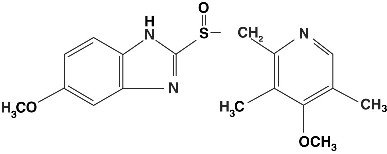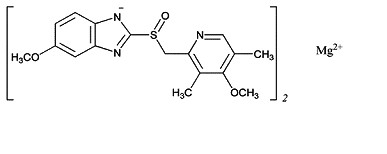 DRUG LABEL: PRILOSEC
NDC: 16590-334 | Form: CAPSULE
Manufacturer: STAT RX USA LLC
Category: prescription | Type: HUMAN PRESCRIPTION DRUG LABEL
Date: 20100219

ACTIVE INGREDIENTS: OMEPRAZOLE MAGNESIUM 20 mg/1 1
INACTIVE INGREDIENTS: FD&C BLUE NO. 2

11 DESCRIPTION

The active ingredient in PRILOSEC (omeprazole) Delayed-Release Capsules is a substituted benzimidazole, 5-methoxy-2-[[(4-methoxy-3, 5-dimethyl-2-pyridinyl) methyl] sulfinyl]-1H-benzimidazole, a compound that inhibits gastric acid secretion. Its empirical formula is C17H19N3O3S, with a molecular weight of 345.42. The structural formula is:

STRUCTURE IMAGE

Omeprazole is a white to off-white crystalline powder that melts with decomposition at about 155°C. It is a weak base, freely soluble in ethanol and methanol, and slightly soluble in acetone and isopropanol and very slightly soluble in water. The stability of omeprazole is a function of pH; it is rapidly degraded in acid media, but has acceptable stability under alkaline conditions.

The active ingredient in PRILOSEC (omeprazole magnesium) for Delayed Release Oral Suspension, is 5-Methoxy-2-[[(4-methoxy-3,5-dimethyl-2-pyridinyl)methyl]sulfinyl]-1H-benzimidazole, magnesium salt (2:1)

Omeprazole magnesium is a white to off white powder with a melting point with degradation at 200°C. The salt is slightly soluble (0.25 mg/ml) in water at 25°C, and it is soluble in methanol. The half-life is highly pH dependent.

The empirical formula for omeprazole magnesium is (C17H18N3O3S)2 Mg, the molecular weight is 713.12 and the structural formula is

STRUCTURE IMAGE 2

PRILOSEC is supplied as delayed-release capsules for oral administration. Each delayed-release capsule contains either 10 mg, 20 mg or 40 mg of omeprazole in the form of enteric-coated granules with the following inactive ingredients: cellulose, disodium hydrogen phosphate, hydroxypropyl cellulose, hypromellose, lactose, mannitol, sodium lauryl sulfate and other ingredients. The capsule shells have the following inactive ingredients: gelatin-NF, FD and C Blue #1, FD and C Red #40, D and C Red #28, titanium dioxide, synthetic black iron oxide, isopropanol, butyl alcohol, FD and C Blue #2, D and C Red #7 Calcium Lake, and, in addition, the 10 mg and 40 mg capsule shells also contain D and C Yellow #10.

Each packet of PRILOSEC For Delayed-Release Oral Suspension contains either 2.8 mg or 11.2 mg of omeprazole magnesium (equivalent to 2.5 mg or 10 mg of omeprazole), in the form of enteric-coated granules with the following inactive ingredients: glyceryl monostearate, hydroxypropyl cellulose, hypromellose, magnesium stearate, methacrylic acid copolymer C, polysorbate, sugar spheres, talc, and triethyl citrate, and also inactive granules. The inactive granules are composed of the following ingredients: citric acid, crospovidone, dextrose, hydroxypropyl cellulose, iron oxide and xantham gum. The omeprazole granules and inactive granules are constituted with water to form a suspension and are given by oral, nasogastric or direct gastric administration.

12 CLINICAL PHARMACOLOGY 12.1 Mechanism of Action

Omeprazole belongs to a class of antisecretory compounds, the substituted benzimidazoles, that suppress gastric acid secretion by specific inhibition of the H^+/K^+ ATPase enzyme system at the secretory surface of the gastric parietal cell. Because this enzyme system is regarded as the acid (proton) pump within the gastric mucosa, omeprazole has been characterized as a gastric acid-pump inhibitor, in that it blocks the final step of acid production. This effect is dose-related and leads to inhibition of both basal and stimulated acid secretion irrespective of the stimulus. Animal studies indicate that after rapid disappearance from plasma, omeprazole can be found within the gastric mucosa for a day or more.

12.2 Pharmacodynamics

Antisecretory Activity

After oral administration, the onset of the antisecretory effect of omeprazole occurs within one hour, with the maximum effect occurring within two hours. Inhibition of secretion is about 50% of maximum at 24 hours and the duration of inhibition lasts up to 72 hours. The antisecretory effect thus lasts far longer than would be expected from the very short (less than one hour) plasma half-life, apparently due to prolonged binding to the parietal H^+/K^+ ATPase enzyme. When the drug is discontinued, secretory activity returns gradually, over 3 to 5 days. The inhibitory effect of omeprazole on acid secretion increases with repeated once-daily dosing, reaching a plateau after four days.

Results from numerous studies of the antisecretory effect of multiple doses of 20 mg and 40 mg of omeprazole in normal volunteers and patients are shown below. The “max” value represents determinations at a time of maximum effect (2-6 hours after dosing), while “min” values are those 24 hours after the last dose of omeprazole.

Single daily oral doses of omeprazole ranging from a dose of 10 mg to 40 mg have produced 100% inhibition of 24-hour intragastric acidity in some patients.

Serum Gastric Effects

In studies involving more than 200 patients, serum gastrin levels increased during the first 1 to 2 weeks of once-daily administration of therapeutic doses of omeprazole in parallel with inhibition of acid secretion. No further increase in serum gastrin occurred with continued treatment. In comparison with histamine H2-receptor antagonists, the median increases produced by 20 mg doses of omeprazole were higher (1.3 to 3.6 fold vs. 1.1 to 1.8 fold increase). Gastrin values returned to pretreatment levels, usually within 1 to 2 weeks after discontinuation of therapy.

Enterochromaffin-like (ECL) Cell Effects

Human gastric biopsy specimens have been obtained from more than 3000 patients treated with omeprazole in long-term clinical trials. The incidence of ECL cell hyperplasia in these studies increased with time; however, no case of ECL cell carcinoids, dysplasia, or neoplasia has been found in these patients. [See Clinical Pharmacology (12 ] However, these studies are of insufficient duration and size to rule out the possible influence of long-term administration of omeprazole on the development of any premalignant or malignant conditions.

Other Effects

Systemic effects of omeprazole in the CNS, cardiovascular and respiratory systems have not been found to date. Omeprazole, given in oral doses of 30 or 40 mg for 2 to 4 weeks, had no effect on thyroid function, carbohydrate metabolism, or circulating levels of parathyroid hormone, cortisol, estradiol, testosterone, prolactin, cholecystokinin or secretin.

No effect on gastric emptying of the solid and liquid components of a test meal was demonstrated after a single dose of omeprazole 90 mg. In healthy subjects, a single I.V. dose of omeprazole (0.35 mg/kg) had no effect on intrinsic factor secretion. No systematic dose-dependent effect has been observed on basal or stimulated pepsin output in humans.

However, when intragastric pH is maintained at 4.0 or above, basal pepsin output is low, and pepsin activity is decreased.

As do other agents that elevate intragastric pH, omeprazole administered for 14 days in healthy subjects produced a significant increase in the intragastric concentrations of viable bacteria. The pattern of the bacterial species was unchanged from that commonly found in saliva. All changes resolved within three days of stopping treatment.

The course of Barrett’s esophagus in 106 patients was evaluated in a U.S. double-blind controlled study of PRILOSEC 40 mg twice daily for 12 months followed by 20 mg twice daily for 12 months or ranitidine 300 mg twice daily for 24 months. No clinically significant impact on Barrett’s mucosa by antisecretory therapy was observed. Although neosquamous epithelium developed during antisecretory therapy, complete elimination of Barrett’s mucosa was not achieved. No significant difference was observed between treatment groups in development of dysplasia in Barrett’s mucosa and no patient developed esophageal carcinoma during treatment. No significant differences between treatment groups were observed in development of ECL cell hyperplasia, corpus atrophic gastritis, corpus intestinal metaplasia, or colon polyps exceeding 3 mm in diameter [See Clinical Pharmacology (12)].

12.3 Pharmacokinetics

Absorption

PRILOSEC Delayed-Release Capsules contain an enteric-coated granule formulation of omeprazole (because omeprazole is acid-labile), so that absorption of omeprazole begins only after the granules leave the stomach. Absorption is rapid, with peak plasma levels of omeprazole occurring within 0.5 to 3.5 hours. Peak plasma concentrations of omeprazole and AUC are approximately proportional to doses up to 40 mg, but because of a saturable first-pass effect, a greater than linear response in peak plasma concentration and AUC occurs with doses greater than 40 mg. Absolute bioavailability (compared with intravenous administration) is about 30-40% at doses of 20-40 mg, due in large part to presystemic metabolism. In healthy subjects the plasma half-life is 0.5 to 1 hour, and the total body clearance is 500-600 mL/min.

Based on a relative bioavailability study, the AUC and Cmax of PRILOSEC (omeprazole magnesium) for Delayed-Release Oral Suspension were 87% and 88% of those for PRILOSEC Delayed-Release Capsules, respectively.

The bioavailability of omeprazole increases slightly upon repeated administration of PRILOSEC Delayed-Release Capsules.

PRILOSEC Delayed-Release Capsule 40 mg was bioequivalent when administered with and without applesauce. However, PRILOSEC Delayed-Release Capsule 20 mg was not bioequivalent when administered with and without applesauce. When administered with applesauce, a mean 25% reduction in Cmax was observed without a significant change in AUC for PRILOSEC Delayed-Release Capsule 20 mg. The clinical relevance of this finding is unknown.

Distribution

Protein binding is approximately 95%.

Metabolism

Omeprazole is extensively metabolized by the cytochrome P450 (CYP) enzyme system.

Excretion

Following single dose oral administration of a buffered solution of omeprazole, little if any unchanged drug was excreted in urine. The majority of the dose (about 77%) was eliminated in urine as at least six metabolites. Two were identified as hydroxyomeprazole and the corresponding carboxylic acid. The remainder of the dose was recoverable in feces. This implies a significant biliary excretion of the metabolites of omeprazole. Three metabolites have been identified in plasma — the sulfide and sulfone derivatives of omeprazole, and hydroxyomeprazole. These metabolites have very little or no antisecretory activity.

Combination Therapy with Antimicrobials

Omeprazole 40 mg daily was given in combination with clarithromycin 500 mg every 8 hours to healthy adult male subjects. The steady state plasma concentrations of omeprazole were increased (Cmax, AUC0-24, and T1/2 increases of 30%, 89% and 34% respectively) by the concomitant administration of clarithromycin. The observed increases in omeprazole plasma concentration were associated with the following pharmacological effects. The mean 24-hour gastric pH value was 5.2 when omeprazole was administered alone and 5.7 when co-administered with clarithromycin.

The plasma levels of clarithromycin and 14-hydroxy-clarithromycin were increased by the concomitant administration of omeprazole. For clarithromycin, the mean Cmax was 10% greater, the mean Cmin was 27% greater, and the mean AUC0-8 was 15% greater when clarithromycin was administered with omeprazole than when clarithromycin was administered alone. Similar results were seen for 14-hydroxy-clarithromycin, the mean Cmax was 45% greater, the mean Cmin was 57% greater, and the mean AUC0-8 was 45% greater. Clarithromycin concentrations in the gastric tissue and mucus were also increased by concomitant administration of omeprazole.

Special Populations

Geriatric Population

The elimination rate of omeprazole was somewhat decreased in the elderly, and bioavailability was increased. Omeprazole was 76% bioavailable when a single 40 mg oral dose of omeprazole (buffered solution) was administered to healthy elderly volunteers, versus 58% in young volunteers given the same dose. Nearly 70% of the dose was recovered in urine as metabolites of omeprazole and no unchanged drug was detected. The plasma clearance of omeprazole was 250 mL/min (about half that of young volunteers) and its plasma half-life averaged one hour, about twice that of young healthy volunteers.

Pediatric Use

The pharmacokinetics of omeprazole have been investigated in pediatric patients 2 to 16 years of age:

Following comparable mg/kg doses of omeprazole, younger children (2 to 5 years of age) have lower AUCs than children 6 to16 years of age or adults; AUCs of the latter two groups did not differ. [See Dosage and Administration (2) ]

Hepatic Impairment

In patients with chronic hepatic disease, the bioavailability increased to approximately 100% compared with an I.V. dose, reflecting decreased first-pass effect, and the plasma half-life of the drug increased to nearly 3 hours compared with the half-life in normals of 0.5-1 hour. Plasma clearance averaged 70 mL/min, compared with a value of 500-600 mL/min in normal subjects. Dose reduction, particularly where maintenance of healing of erosive esophagitis is indicated, for the hepatically impaired should be considered.

Renal Impairment

In patients with chronic renal impairment, whose creatinine clearance ranged between 10 and 62 mL/min/1.73 m^2, the disposition of omeprazole was very similar to that in healthy volunteers, although there was a slight increase in bioavailability. Because urinary excretion is a primary route of excretion of omeprazole metabolites, their elimination slowed in proportion to the decreased creatinine clearance. No dose reduction is necessary in patients with renal impairment.

Asian Population

In pharmacokinetic studies of single 20 mg omeprazole doses, an increase in AUC of approximately four-fold was noted in Asian subjects compared with Caucasians. Dose reduction, particularly where maintenance of healing of erosive esophagitis is indicated, for Asian subjects should be considered.

12.4 Microbiology

Omeprazole and clarithromycin dual therapy and omeprazole, clarithromycin and amoxicillin triple therapy have been shown to be active against most strains of Helicobacter pylori in vitro and in clinical infections as described in the Indications and Usage section (1.1).

Helicobacter

Helicobacter pylori- Pretreatment Resistance

Clarithromycin pretreatment resistance rates were 3.5% (4/113) in the omeprazole/clarithromycin dual therapy studies (4 and 5) and 9.3% (41/439) in omeprazole/clarithromycin/amoxicillin triple therapy studies (1, 2, and 3).

Amoxicillin pretreatment susceptible isolates (≤ 0.25 µg/mL) were found in 99.3% (436/439) of the patients in the omeprazole/clarithromycin/amoxicillin triple therapy studies (1, 2, and 3). Amoxicillin pretreatment minimum inhibitory concentrations (MICs) > 0.25 µg/mL occurred in 0.7% (3/439) of the patients, all of whom were in the clarithromycin and amoxicillin study arm. One patient had an unconfirmed pretreatment amoxicillin minimum inhibitory concentration (MIC) of > 256 µg/mL by Etest®.

Patients not eradicated of H. pylori following omeprazole/clarithromycin/amoxicillin triple therapy or omeprazole/clarithromycin dual therapy will likely have clarithromycin resistant H. pylori isolates. Therefore, clarithromycin susceptibility testing should be done, if possible. Patients with clarithromycin resistant H. pylori should not be treated with any of the following: omeprazole/clarithromycin dual therapy, omeprazole/clarithromycin/amoxicillin triple therapy, or other regimens which include clarithromycin as the sole antimicrobial agent.

Amoxicillin Susceptibility Test Results and Clinical/Bacteriological Outcomes

In the triple therapy clinical trials, 84.9% (157/185) of the patients in the omeprazole/clarithromycin/amoxicillin treatment group who had pretreatment amoxicillin susceptible MICs (≤ 0.25 µg/mL) were eradicated of H. pylori and 15.1% (28/185) failed therapy. Of the 28 patients who failed triple therapy, 11 had no post-treatment susceptibility test results and 17 had post-treatment H. pylori isolates with amoxicillin susceptible MICs. Eleven of the patients who failed triple therapy also had post-treatment H. pylori isolates with clarithromycin resistant MICs.

Susceptibility Test for Helicobacter pylori

The reference methodology for susceptibility testing of H. pylori is agar dilution MICs^1. One to three microliters of an inoculum equivalent to a No. 2 McFarland standard (1 x 10^7 - 1 x 10^8 CFU/mL for H. pylori) are inoculated directly onto freshly prepared antimicrobial containing Mueller-Hinton agar plates with 5% aged defibrinated sheep blood (≥ 2 weeks old). The agar dilution plates are incubated at 35°C in a microaerobic environment produced by a gas generating system suitable for campylobacters. After 3 days of incubation, the MICs are recorded as the lowest concentration of antimicrobial agent required to inhibit growth of the organism. The clarithromycin and amoxicillin MIC values should be interpreted according to the following criteria:

INDICATIONS AND USAGE

1 INDICATIONS AND USAGE 1.1 Duodenal Ulcer (adults)

PRILOSEC is indicated for short-term treatment of active duodenal ulcer in adults. Most patients heal within four weeks. Some patients may require an additional four weeks of therapy.

PRILOSEC in combination with clarithromycin and amoxicillin, is indicated for treatment of patients with H. pylori infection and duodenal ulcer disease (active or up to 1-year history) to eradicate H. pylori in adults.

PRILOSEC, in combination with clarithromycin is indicated for treatment of patients with H. pylori infection and duodenal ulcer disease to eradicate H. pylori in adults.

Eradication of H. pylori has been shown to reduce the risk of duodenal ulcer recurrence [see Clinical Studies (14.1) and Dosage and Administration (2) ].

Among patients who fail therapy, PRILOSEC with clarithromycin is more likely to be associated with the development of clarithromycin resistance as compared with triple therapy. In patients who fail therapy, susceptibility testing should be done. If resistance to clarithromycin is demonstrated or susceptibility testing is not possible, alternative antimicrobial therapy should be instituted. [See Microbiology section (12.4)], and the clarithromycin package insert, Microbiology section.)

1.2 Gastric Ulcer (adults)

PRILOSEC is indicated for short-term treatment (4-8 weeks) of active benign gastric ulcer in adults. [See Clinical Studies (14.2) ]

1.3 Treatment of Gastroesophageal Reflux Disease (GERD) (adults and pediatric patients)

Symptomatic GERD

PRILOSEC is indicated for the treatment of heartburn and other symptoms associated with GERD in pediatric patients and adults.

Erosive Esophagitis

PRILOSEC is indicated for the short-term treatment (4-8 weeks) of erosive esophagitis that has been diagnosed by endoscopy in pediatric patients and adults. [See Clinical Studies (14.4) ]

The efficacy of PRILOSEC used for longer than 8 weeks in these patients has not been established. If a patient does not respond to 8 weeks of treatment, an additional 4 weeks of treatment may be given. If there is recurrence of erosive esophagitis or GERD symptoms (eg, heartburn), additional 4-8 week courses of omeprazole may be considered.

1.4 Maintenance of Healing of Erosive Esophagitis (adults and pediatric patients)

PRILOSEC is indicated to maintain healing of erosive esophagitis in pediatric patients and adults.

Controlled studies do not extend beyond 12 months. [See Clinical Studies (14.4) ]

1.5 Pathological Hypersecretory Conditions (adults)

PRILOSEC is indicated for the long-term treatment of pathological hypersecretory conditions (eg, Zollinger-Ellison syndrome, multiple endocrine adenomas and systemic mastocytosis) in adults.

4 CONTRAINDICATIONS

PRILOSEC Delayed-Release Capsules are contraindicated in patients with known hypersensitivity to any component of the formulation. Hypersensitivity reactions may include anaphylaxis, anaphylactic shock, angioedema, bronchospasm, interstitial nephritis, and urticaria [see Adverse Reactions (6)].

ADVERSE REACTIONS

6 ADVERSE REACTIONS 6.1 Clinical Trials Experience with PRILOSEC Monotherapy

Because clinical trials are conducted under widely varying conditions, adverse reaction rates observed in the clinical trials of a drug cannot be directly compared to rates in the clinical trials of another drug and may not reflect the rates observed in practice.

The safety data described below reflects exposure to PRILOSEC Delayed-Release Capsules in 3096 patients from worldwide clinical trials (465 patients from US studies and 2,631 patients from international studies). Indications clinically studied in US trials included duodenal ulcer, resistant ulcer, and Zollinger-Ellison syndrome. The international clinical trials were double blind and open-label in design. The most common adverse reactions reported (i.e., with an incidence rate greater or equal to 2%) from PRILOSEC-treated patients enrolled in these studies included headache (6.9%), abdominal pain (5.2%), nausea (4.0%), diarrhea (3.7%), vomiting (3.2%), and flatulence (2.7%).

Additional adverse reactions that were reported with an incidence ≥1% included acid regurgitation (1.9%), upper respiratory infection (1.9%), constipation (1.5%), dizziness (1.5%), rash (1.5%), asthenia (1.3%), back pain (1.1%), and cough (1.1%).

The clinical trial safety profile in patients greater than 65 years of age was similar to that in patients 65 years of age or less.

The clinical trial safety profile in pediatric patients who received PRILOSEC Delayed-Release Capsules was similar to that in adult patients. Unique to the pediatric population, however, adverse reactions of the respiratory system were most frequently reported in both the 1 to greater than 2 and 2 to 16 year age groups (75.0% and 18.5%, respectively). Similarly, fever was frequently reported in the 1 to 2 year age group (33.0%) and accidental injuries were reported frequently in the 2 to 16 year age group (3.8%). [See Use in Specific Populations (8.4) ]

6.2 Clinical Trials Experience with PRILOSEC in Combination Therapy for H. pylori Eradication

In clinical trials using either dual therapy with PRILOSEC and clarithromycin, or triple therapy with PRILOSEC, clarithromycin, and amoxicillin, no adverse reactions unique to these drug combinations were observed. Adverse reactions observed were limited to those previously reported with omeprazole, clarithromycin, or amoxicillin alone.

Dual Therapy (PRILOSEC/clarithromycin)

Adverse reactions observed in controlled clinical trials using combination therapy with PRILOSEC and clarithromycin (n = 346) that differed from those previously described for PRILOSEC alone were taste perversion (15%), tongue discoloration (2%), rhinitis (2%), pharyngitis (1%) and flu-syndrome (1%). (For more information on clarithromycin, refer to the clarithromycin prescribing information, Adverse Reactions section).

Triple Therapy (PRILOSEC/clarithromycin/amoxicillin)

The most frequent adverse reactions observed in clinical trials using combination therapy with PRILOSEC, clarithromycin, and amoxicillin (n = 274) were diarrhea (14%), taste perversion (10%), and headache (7%). None of these occurred at a higher frequency than that reported by patients taking antimicrobial agents alone. (For more information on clarithromycin or amoxicillin, refer to the respective prescribing information, Adverse Reactions sections).

6.3 Post-marketing Experience

The following adverse reactions have been identified during post-approval use of PRILOSEC Delayed-Release Capsules. Because these reactions are voluntarily reported from a population of uncertain size, it is not always possible to reliably estimate their actual frequency or establish a causal relationship to drug exposure.

Body As a Whole: Hypersensitivity reactions including anaphylaxis, anaphylactic shock, angioedema, bronchospasm, interstitial nephritis, urticaria, (see also Skin below); fever; pain; fatigue; malaise;

Cardiovascular: Chest pain or angina, tachycardia, bradycardia, palpitations, elevated blood pressure, peripheral edema

Endocrine: Gynecomastia

Gastrointestinal: Pancreatitis (some fatal), anorexia, irritable colon, fecal discoloration, esophageal candidiasis, mucosal atrophy of the tongue, stomatitis, abdominal swelling, dry mouth. During treatment with omeprazole, gastric fundic gland polyps have been noted rarely. These polyps are benign and appear to be reversible when treatment is discontinued. Gastroduodenal carcinoids have been reported in patients with ZE syndrome on long-term treatment with PRILOSEC. This finding is believed to be a manifestation of the underlying condition, which is known to be associated with such tumors.

Hepatic: Liver disease including hepatic failure (some fatal), liver necrosis (some fatal), hepatic encephalopathy hepatocellular disease, cholestatic disease, mixed hepatitis, jaundice, and elevations of liver function tests [ALT, AST, GGT, alkaline phosphatase, and bilirubin]

Metabolic/Nutritional: Hypoglycemia, hyponatremia, weight gain

Musculoskeletal: Muscle weakness, myalgia, muscle cramps, joint pain, leg pain

Nervous System/Psychiatric: Psychiatric and sleep disturbances including depression, agitation, aggression, hallucinations, confusion, insomnia, nervousness, apathy, somnolence, anxiety, and dream abnormalities; tremors, paresthesia; vertigo

Respiratory: Epistaxis, pharyngeal pain

Skin: Severe generalized skin reactions including toxic epidermal necrolysis (some fatal), Stevens-Johnson syndrome, and erythema multiforme; photosensitivity; urticaria; rash; skin inflammation; pruritus; petechiae; purpura; alopecia; dry skin; hyperhidrosis

Special Senses: Tinnitus, taste perversion

Ocular: Optic atrophy, anterior ischemic optic neuropathy, optic neuritis, dry eye syndrome, ocular irritation, blurred vision, double vision

Urogenital: Interstitial nephritis, hematuria, proteinuria, elevated serum creatinine, microscopic pyuria, urinary tract infection, glycosuria, urinary frequency, testicular pain

Hematologic: Agranulocytosis (some fatal), hemolytic anemia, pancytopenia, neutropenia, anemia, thrombocytopenia, leukopenia, leucocytosis

WARNINGS AND PRECAUTIONS

5. WARNINGS AND PRECAUTIONS 5.1 Concomitant Gastric Malignancy

Symptomatic response to therapy with omeprazole does not preclude the presence of gastric malignancy.

5.2 Atrophic Gastritis

Atrophic gastritis has been noted occasionally in gastric corpus biopsies from patients treated long-term with omeprazole.

5.3 Combiniation Use of PRILOSEC with Amoxicillin

Serious and occasionally fatal hypersensitivity (anaphylactic) reactions have been reported in patients on penicillin therapy. These reactions are more likely to occur in individuals with a history of penicillin hypersensitivity and/or a history of sensitivity to multiple allergens. Before initiating therapy with amoxicillin, careful inquiry should be made concerning previous hypersensitivity reactions to penicillins, cephalosporins or other allergens. If an allergic reaction occurs, amoxicillin should be discontinued and appropriate therapy instituted. Serious anaphylactic reactions require immediate emergency treatment with epinephrine. Oxygen, intravenous steroids and airway management, including intubation, should also be administered as indicated.

Pseudomembranous colitis has been reported with nearly all antibacterial agents and may range in severity from mild to life-threatening. Therefore, it is important to consider this diagnosis in patients who present with diarrhea subsequent to the administration of antibacterial agents.

Treatment with antibacterial agents alters the normal flora of the colon and may permit overgrowth of clostridia. Studies indicate that a toxin produced by Clostridium difficile is a primary cause of “antibiotic-associated colitis.”

After the diagnosis of pseudomembranous colitis has been established, therapeutic measures should be initiated. Mild cases of pseudomembranous colitis usually respond to discontinuation of the drug alone. In moderate to severe cases, consideration should be given to management with fluids and electrolytes, protein supplementation, and treatment with an antibacterial drug clinically effective against Clostridium difficile colitis.

5.4 Combination Use of PRILOSEC with Clarithromycin

Clarithromycin should not be used in pregnant women except in clinical circumstances where no alternative therapy is appropriate. If pregnancy occurs while taking clarithromycin, the patient should be apprised of the potential hazard to the fetus. (See Warnings in prescribing information for clarithromycin.)

Co-administration of omeprazole and clarithromycin has resulted in increases in plasma levels of omeprazole, clarithromycin, and 14-hydroxy-clarithromycin. [See Clinical Pharmacology (12) ]

Concomitant administration of clarithromycin with cisapride or pimozide, is contraindicated.

10 OVERDOSAGE

Reports have been received of overdosage with omeprazole in humans. Doses ranged up to 2400 mg (120 times the usual recommended clinical dose). Manifestations were variable, but included confusion, drowsiness, blurred vision, tachycardia, nausea, vomiting, diaphoresis, flushing, headache, dry mouth, and other adverse reactions similar to those seen in normal clinical experience. [See Adverse Reactions (6)] Symptoms were transient, and no serious clinical outcome has been reported when PRILOSEC was taken alone. No specific antidote for omeprazole overdosage is known. Omeprazole is extensively protein bound and is, therefore, not readily dialyzable. In the event of overdosage, treatment should be symptomatic and supportive.

As with the management of any overdose, the possibility of multiple drug ingestion should be considered. For current information on treatment of any drug overdose, contact a Poison Control Center at 1-800-222-1222.

Single oral doses of omeprazole at 1350, 1339, and 1200 mg/kg were lethal to mice, rats, and dogs, respectively. Animals given these doses showed sedation, ptosis, tremors, convulsions, and decreased activity, body temperature, and respiratory rate and increased depth of respiration.

2 DOSAGE AND ADMINISTRATION

PRILOSEC Delayed-Release Capsules should be taken before eating. In the clinical trials, antacids were used concomitantly with PRILOSEC.

Patients should be informed that the PRILOSEC Delayed-Release Capsule should be swallowed whole.

For patients unable to swallow an intact capsule, alternative administration options are available. [See Dosage and Administration (2.8)]

2.1 Short-Term Treatment of Active Duodenal Ulcer

The recommended adult oral dose of PRILOSEC is 20 mg once daily. Most patients heal within four weeks. Some patients may require an additional four weeks of therapy.

2.2 H. pylori Eradication for the Reduction of the Risk of Duodenal Ulcer Recurrence

Triple Therapy (PRILOSEC/clarithromycin/amoxicillin) — The recommended adult oral regimen is PRILOSEC 20 mg plus clarithromycin 500 mg plus amoxicillin 1000 mg each given twice daily for 10 days. In patients with an ulcer present at the time of initiation of therapy, an additional 18 days of PRILOSEC 20 mg once daily is recommended for ulcer healing and symptom relief.

Dual Therapy (PRILOSEC/clarithromycin) — The recommended adult oral regimen is PRILOSEC 40 mg once daily plus clarithromycin 500 mg three times daily for 14 days. In patients with an ulcer present at the time of initiation of therapy, an additional 14 days of PRILOSEC 20 mg once daily is recommended for ulcer healing and symptom relief.

2.3 Gastric Ulcer

The recommended adult oral dose is 40 mg once daily for 4-8 weeks.

2.4 Gastroesophageal Reflux Disease (GERD)

The recommended adult oral dose for the treatment of patients with symptomatic GERD and no esophageal lesions is 20 mg daily for up to 4 weeks. The recommended adult oral dose for the treatment of patients with erosive esophagitis and accompanying symptoms due to GERD is 20 mg daily for 4 to 8 weeks.

2.5 Maintenance of Healing of Erosive Esophagitis

The recommended adult oral dose is 20 mg daily. [See Clinical Studies (14.4) ]

2.6 Pathological Hypersecretory Conditions

The dosage of PRILOSEC in patients with pathological hypersecretory conditions varies with the individual patient. The recommended adult oral starting dose is 60 mg once daily. Doses should be adjusted to individual patient needs and should continue for as long as clinically indicated. Doses up to 120 mg three times daily have been administered. Daily dosages of greater than 80 mg should be administered in divided doses. Some patients with Zollinger-Ellison syndrome have been treated continuously with PRILOSEC for more than 5 years.

2.7 Pediatric Patients

For the treatment of GERD and maintenance of healing of erosive esophagitis, the recommended daily dose for pediatric patients– 1 to 16 years of age is as follows:

On a per kg basis, the doses of omeprazole required to heal erosive esophagitis in pediatric patients are greater than those for adults.

Alternative administrative options can be used for pediatric patients unable to swallow an intact capsule [See Dosage and Administration (2.8) ].

2.8 Alternative Administration Options

PRILOSEC is available as a delayed-release capsule or as a delayed-release oral suspension.

For patients who have difficulty swallowing capsules, the contents of a PRILOSEC Delayed-Release Capsule can be added to applesauce. One tablespoon of applesauce should be added to an empty bowl and the capsule should be opened. All of the pellets inside the capsule should be carefully emptied on the applesauce. The pellets should be mixed with the applesauce and then swallowed immediately with a glass of cool water to ensure complete swallowing of the pellets. The applesauce used should not be hot and should be soft enough to be swallowed without chewing. The pellets should not be chewed or crushed. The pellets/applesauce mixture should not be stored for future use.

PRILOSEC For Delayed-Release Oral Suspension should be administered as follows:

- Empty the contents of a 2.5 mg packet into a container containing 5 mL of water.
- Empty the contents of a 10 mg packet into a container containing 15 mL of water.
- Stir
- Leave 2 to 3 minutes to thicken.
- Stir and drink within 30 minutes.
- If any material remains after drinking, add more water, stir and drink immediately.

For patients with a nasogastric or gastric tube in place:

- Add 5 mL of water to a catheter tipped syringe and then add the contents of a 2.5 mg packet (or 15 mL of water for the 10 mg packet). It is important to only use a catheter tipped syringe when administering PRILOSEC through a nasogastric tube or gastric tube.
- Immediately shake the syringe and leave 2 to 3 minutes to thicken.
- Shake the syringe and inject through the nasogastric or gastric tube, French size 6 or larger, into the stomach within 30 minutes.
- Refill the syringe with an equal amount of water.
- Shake and flush any remaining contents from the nasogastric or gastric tube into the stomach.

16 HOW SUPPLIED/STORAGE AND HANDLING

PRILOSEC Delayed-Release Capsules, 10 mg, are opaque, hard gelatin, apricot and amethyst colored capsules, coded 606 on cap and PRILOSEC 10 on the body. They are supplied as follows:

NDC 0186-0606-31 unit of use bottles of 30

PRILOSEC Delayed-Release Capsules, 20 mg, are opaque, hard gelatin, amethyst colored capsules, coded 742 on cap and PRILOSEC 20 on body. They are supplied as follows:

NDC 0186-0742-31 unit of use bottles of 30

NDC 0186-0742-82 bottles of 1000.

PRILOSEC Delayed-Release Capsules, 40 mg, are opaque, hard gelatin, apricot and amethyst colored capsules, coded 743 on cap and PRILOSEC 40 on the body. They are supplied as follows:

NDC 0186-0743-31 unit of use bottles of 30

NDC 0186-0743-68 bottles of 100

PRILOSEC For Delayed-Release Oral Suspension, 2.5 mg or 10 mg, is supplied as a unit dose packet containing a fine yellow powder, consisting of white to brownish omeprazole granules and pale yellow inactive granules. PRILOSEC unit dose packets are supplied as follows:

NDC 0186-0625–01 unit dose packages of 30: 2.5 mg packets

NDC 0186-0610–01 unit dose packages of 30: 10 mg packets

Storage

Store PRILOSEC Delayed-Release Capsules in a tight container protected from light and moisture. Store between 15°C and 30°C (59°F and 86°F).

Store PRILOSEC For Delayed-Release Oral Suspension at 25°C (77°F); excursions permitted to 15 – 30°C (59 – 86°F). [See USP Controlled Room Temperature].

17 PATIENT COUNSELING INFORMATION

PRILOSEC should be taken before eating. Patients should be informed that the PRILOSEC Delayed-Release Capsule should be swallowed whole.

For patients who have difficulty swallowing capsules, the contents of a PRILOSEC Delayed-Release Capsule can be added to applesauce. One tablespoon of applesauce should be added to an empty bowl and the capsule should be opened. All of the pellets inside the capsule should be carefully emptied on the applesauce. The pellets should be mixed with the applesauce and then swallowed immediately with a glass of cool water to ensure complete swallowing of the pellets. The applesauce used should not be hot and should be soft enough to be swallowed without chewing. The pellets should not be chewed or crushed. The pellets/applesauce mixture should not be stored for future use.

PRILOSEC For Delayed-Release Oral Suspension should be administered as follows:

- Empty the contents of a 2.5 mg packet into a container containing 5 mL of water.
- Empty the contents of a 10 mg packet into a container containing 15 mL of water.
- Stir
- Leave 2 to 3 minutes to thicken.
- Stir and drink within 30 minutes.
- If any material remains after drinking, add more water, stir and drink immediately.

For patients with a nasogastric or gastric tube in place:

- Add 5 mL of water to a catheter tipped syringe and then add the contents of a 2.5 mg packet (or 15 mL of water for the 10 mg packet). It is important to only use a catheter tipped syringe when administering PRILOSEC through a nasogastric tube or gastric tube.
- Immediately shake the syringe and leave 2 to 3 minutes to thicken.
- Shake the syringe and inject through the nasogastric or gastric tube, French size 6 or larger, into the stomach within 30 minutes.
- Refill the syringe with an equal amount of water.
- Shake and flush any remaining contents from the nasogastric or gastric tube into the stomach.

PRILOSEC is a trademark of the AstraZeneca group of companies.

©AstraZeneca 2008

Manufactured for: AstraZeneca LP, Wilmington, DE 19850

PRILOSEC For Delayed-Release Oral Suspension is a Product of Sweden

91941XX

31090-XX

LABEL IMAGE